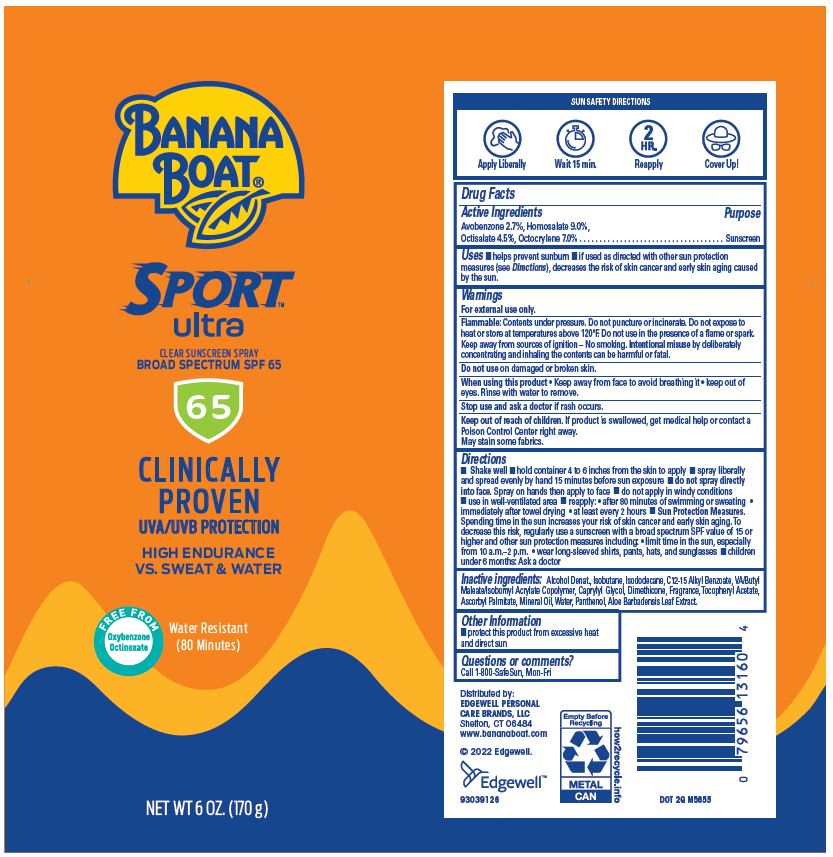 DRUG LABEL: Banana Boat Sport Ultra Clear Sunscreen Broad Spectrum SPF 65
NDC: 63354-634 | Form: AEROSOL, SPRAY
Manufacturer: Edgewell Personal Care Brands LLC
Category: otc | Type: HUMAN OTC DRUG LABEL
Date: 20251202

ACTIVE INGREDIENTS: HOMOSALATE 9 g/100 g; OCTISALATE 4.5 g/100 g; AVOBENZONE 2.7 g/100 g; OCTOCRYLENE 7 g/100 g
INACTIVE INGREDIENTS: ALCOHOL; CAPRYLYL GLYCOL; DIMETHICONE; ISOBUTANE; ALKYL (C12-15) BENZOATE; ISODODECANE; .ALPHA.-TOCOPHEROL ACETATE; ALOE VERA LEAF; MINERAL OIL; PANTHENOL; ASCORBYL PALMITATE; WATER

Active Ingredients

Avobenzone 2.7%, Homosalate 9.0%, Octisalate 4.5%, Octocrylene 7.0% .

Purpose

Sunscreen

Uses

- helps prevent sunburn
- if used as directed with other sun protection measures (see Directions), decreases the risk of skin cancer and early skin aging caused by the sun

Warnings

For external use only.

Flammable: Contents under pressure. Do not puncture or incinerate. Do not expose to heat or store at temperatures above 120°F. Do not use in the presence of a flame or spark. Keep away from sources of ignition – No smoking. Intentional misuse by deliberately
concentrating and inhaling the contents can be harmful or fatal.

May stain some fabrics.

Do not use

on damaged or broken skin.

When using this product

• Keep away from face to avoid breathing it • keep out of eyes. Rinse with water to remove.

Stop use and ask a doctor

if rash occurs.

Keep out of reach of children

If product is swallowed, get medical help or contact a Poison Control Center right away.

Directions

• Shake well • hold container 4 to 6 inches from the skin to apply • spray liberally and spread evenly by hand 15 minutes before sun exposure • do not spray directly into face. Spray on hands then apply to face •do not apply in windy conditions • use in well-ventilated area • reapply: • after 80 minutes of swimming or sweating • immediately after towel drying • at least every 2 hours • Sun Protection Measures. Spending time in the sun increases your risk of skin cancer and early skin aging. To decrease this risk, regularly use a sunscreen with a broad spectrum SPF value of 15 or higher and other sun protection measures including: • limit time in the sun, especially from 10 a.m.–2 p.m. • wear long-sleeved shirts, pants, hats, and sunglasses • children under 6 months: Ask a doctor

Inactive ingredients:

Alcohol Denat., Isobutane, Isododecane, C12-15 Alkyl Benzoate, VA/Butyl Maleate/Isobornyl Acrylate Copolymer, Caprylyl Glycol, Dimethicone, Fragrance, Tocopheryl Acetate, Ascorbyl Palmitate, Mineral Oil, Water, Panthenol, Aloe Barbadensis Leaf Extract.

Other Information

• protect this product from excessive heat and direct sun

Questions or comments?

Call 1-800-SafeSun, Mon-Fri

Principal Display Panel

BANANA
BOAT®
SPORT
ultra
CLEAR SUNSCREEN SPRAY
BROAD SPECTRUM SPF 65
65
CLINICALLY
PROVEN
UVA/UVB PROTECTION
HIGH ENDURANCE
VS. SWEAT & WATER
FREE FROM
Oxybenzone
Octinoxate
Water Resistant
(80 Minutes)
NET WT 6 OZ. (170 g)